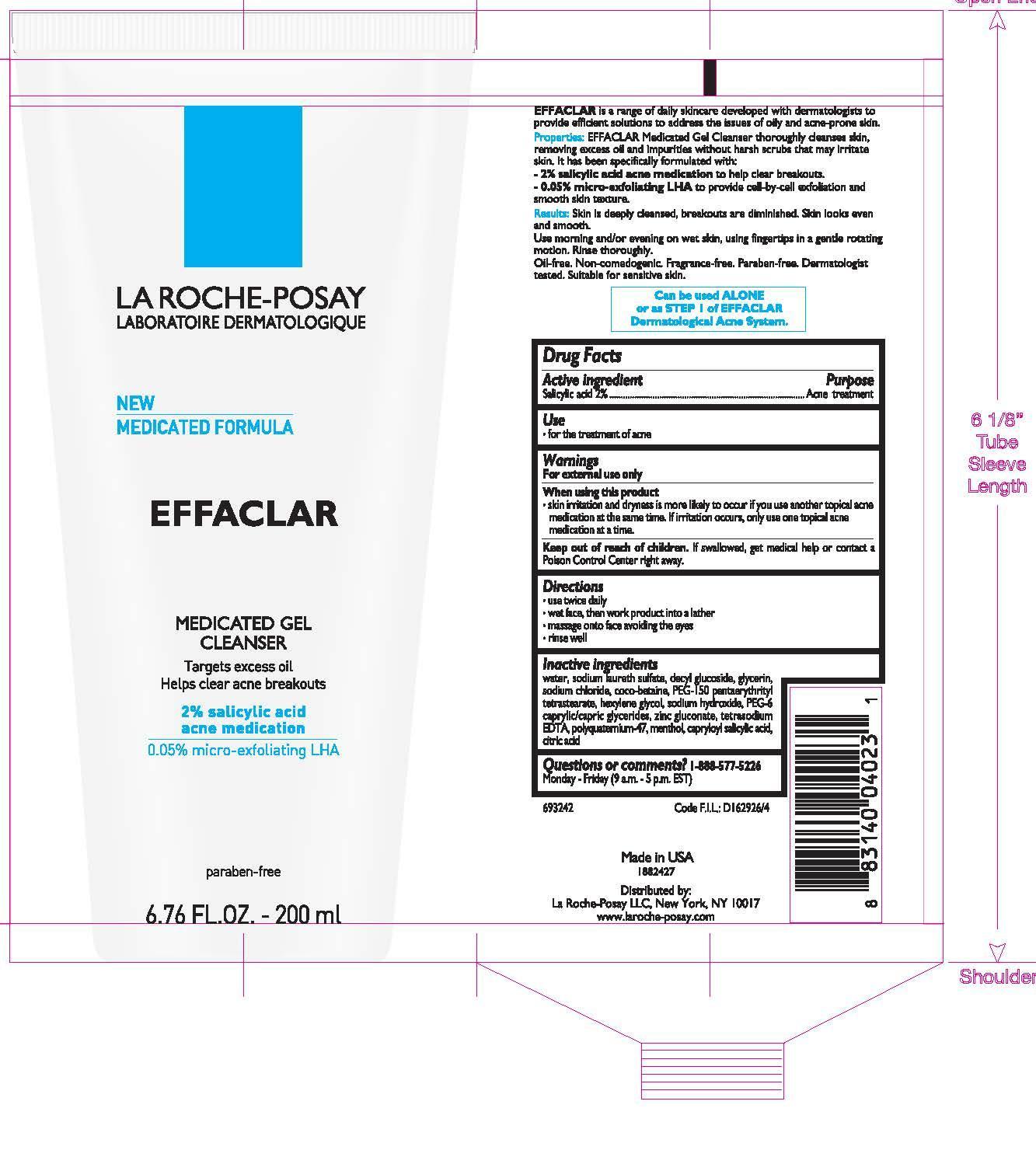 DRUG LABEL: La Roche Posay Laboratorie Dermatologique Effaclar Medicated Cleanser
NDC: 49967-023 | Form: GEL
Manufacturer: L'Oreal USA Products Inc
Category: otc | Type: HUMAN OTC DRUG LABEL
Date: 20231231

ACTIVE INGREDIENTS: SALICYLIC ACID 20 mg/1 mL
INACTIVE INGREDIENTS: WATER; SODIUM LAURETH SULFATE; DECYL GLUCOSIDE; GLYCERIN; SODIUM CHLORIDE; COCO-BETAINE; PEG-150 PENTAERYTHRITYL TETRASTEARATE; HEXYLENE GLYCOL; SODIUM HYDROXIDE; PEG-6 CAPRYLIC/CAPRIC GLYCERIDES; ZINC GLUCONATE; MENTHOL; CAPRYLOYL SALICYLIC ACID

Drug Facts

Active ingredient

Salicylic acid 2%

Purpose

Acne treatment

Use

for the treatment of acne

Warnings

For external use only

When using this product

skin irritation and dryness is more likely to occur if you use another topical acne medication at the same time. If irritation occurs, only use one topical acne medication at a time.

Keep out of reach of children.

If swallowed, get medical help or contact a Poison Control Center right away.

Directions

- use twice daily
- wet face, then work product into a lather
- massage onto face, avoiding the eyes
- rinse well

Inactive ingredients

water, sodium laureth sulfate, decyl glucoside, glycerin, sodium chloride, coco-betaine, PEG-150 pentaerythrityl tetrastearate, hexylene glycol, sodium hydroxide, PEG-6 caprylic/capric glycerides, zinc gluconate, tetrasodium EDTA, polyquaternium-47, menthol, capryloyl salicylic acid, citric acid

Questions or comments?

1-888-577-5226

Monday - Friday (9 a.m. - 5 p.m. EST)